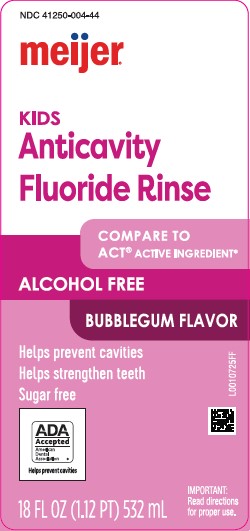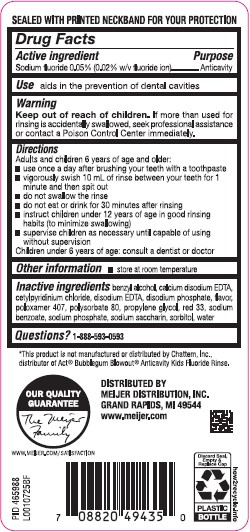 DRUG LABEL: Anticavity Rinse
NDC: 41250-004 | Form: MOUTHWASH
Manufacturer: Meijer, Inc.
Category: otc | Type: HUMAN OTC DRUG LABEL
Date: 20260219

ACTIVE INGREDIENTS: SODIUM FLUORIDE 0.2 mg/1 mL
INACTIVE INGREDIENTS: BENZYL ALCOHOL; EDETATE CALCIUM DISODIUM; CETYLPYRIDINIUM CHLORIDE; EDETATE DISODIUM; MEPREDNISONE DISODIUM PHOSPHATE; POLOXAMER 407; POLYSORBATE 80; PROPYLENE GLYCOL; D&C RED NO. 33; SODIUM BENZOATE; SODIUM PHOSPHATE; SACCHARIN SODIUM; SORBITOL; WATER

Meijer 004.002/004AE
Anticavity Fluoride Rinse, Bubble Gum

Tamper Evident Statement

SEALED WITH PRINTED NECKBAND FOR YOUR PROTECTION

Active ingredient

Sodium fluoride 0.05% (0.02% w/v fluoride ion)

Purpose

Anticavity

Use

aids in the prevention of dental cavities

Warnings

for this product

Keep out of reach of children.

If more than used for rinsing is accidentally swallowed, seek professional assistance or contact a Poison Control Center immediately.

Directions

Adults and children 6 years of age and older:

- use once a day after brushing your teeth with a toothpaste
- vigorously swish 10 milliliters of rinse between your teeth for 1 minute and then spit out
- do not swallow the rinse
- do not eat or drink for 30 minutes after rinsing
- instruct children under 12 years of age in good rinsing habits (to minimize swallowing)
- supervise children as necessary until capable of using without supervision

Children under 6 years of age: consult a dentist or doctor

Other information

- store at room temperature

Inactive ingredients

benzyl alcohol, calcium disodium EDTA, cetylpyridinium chloride, disodium EDTA, disodium phosphate, flavor, poloxamer 407, polysorbate 80, propylene glycol, red 33, sodium benzoate, sodium phosphate, sodium saccharin, sorbitol, water

Questions?

1-888-593-0593

Disclaimer

*This product is not manufactured or distributed by Chattem, Inc., distributor of Act®Bubblegum Blowout®Anticavity Kids Fluoride Rinse.

Adverse reactions

Distributed By

Meijer Distribution, Inc.

Grand Rapids, MI 49544

www.meijer.com

Our Quality Guarantee

www.meijer.com/satisfcation

Discard Seal, Empty & Replace Cap

PLASTIC BOTTLE

how2recycle.info

Principal Panel Display

NDC 41250-004-44

meijer®

Kids

Anticavity

Fluoride Rinse

Compare to ACT®ACTIVE INGREDIENT*

ALCOHOL FREE

BUBBLEGUM FLAVOR

Helps prevent cavities

Helps strengthen teeth

Sugar free

ADA Accepted

American Dental Association

Helps prevent cavities

IMPORTANT: Read directions for proper use.

18 FL OZ (1.12 PT) 532 mL